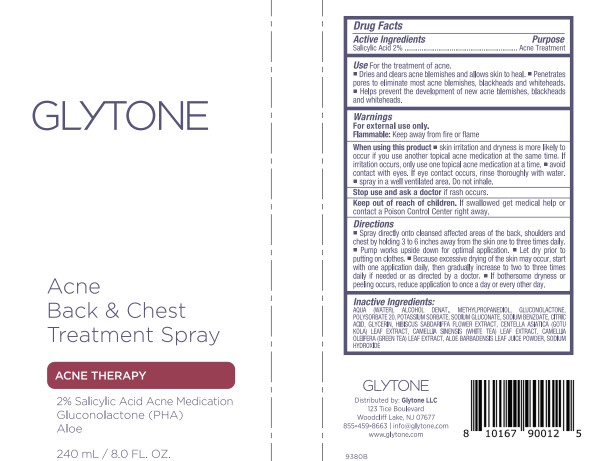 DRUG LABEL: Acne Back Chest Treatment
NDC: 84262-012 | Form: AEROSOL, SPRAY
Manufacturer: GLYTONE LLC
Category: otc | Type: HUMAN OTC DRUG LABEL
Date: 20240628

ACTIVE INGREDIENTS: SALICYLIC ACID 30 mg/1 mL
INACTIVE INGREDIENTS: GLYCERIN; SODIUM BENZOATE; CENTELLA ASIATICA LEAF; HIBISCUS SABDARIFFA FLOWER; POTASSIUM SORBATE; GLUCONOLACTONE; POLYSORBATE 20; SODIUM HYDROXIDE; CITRIC ACID MONOHYDRATE; CALCIUM GLUCONATE; WATER; WHITE TEA; ALCOHOL; METHYLPROPANEDIOL; SODIUM GLUCONATE; CAMELLIA SINENSIS SEED OIL

Glytone Acne Back & Chest Treatment Spray

Active Ingredients

Salicylic Acid 2%

Purpose

Acne Treatment

Use

For the treatment of acne.

- Dries and clears acne blemishes and allows skin to heal.
- Penetrates pores to eliminate most acne blemishes, blackheads and whiteheads.
- Helps prevent the development of new acne blemishes, blackheads and whiteheads.

Warnings

For external use only.

Directions

- Spray directly onto cleansed affected areas of the back, shoulders and chest by holding 3 to 6 inches away from the skin one to three times daily.
- Pump works upside down for optimal application.
- Let dry prior to putting on clothes.
- Beacuase excessive drying of the skin may occur, start with one application daily, then gradually increase to two to three times daily if needed or as directed by a doctor.
- If bothersome dryness or peeling occurs, reduce application to once a day or every other day.

Flammable

Keep away from fire or flame.

When using this product

- skin irritation and dryness is more likely to occur if you use another topical acne medication at the same time. If irritation occurs, only use one topical acne medication at a time.
- avoid contact with eyes. If eye contact occurs, rinse thoroughly with water.
- spray in a well ventilated area. Do not inhale.

Keep out of reach of children.

If swallowed get medical help or contact a Poison Control Center right away.

Inactive Ingredients

AQUA (WATER), ALCOHOL DENAT., METHYLPROPANEDIOL, GLUCONOLACTONE, POLYSORBATE 20, POTASSIUM SORBATE, SODIUM GLUCONATE, SODIUM BENZOATE, CITRIC ACID, GLYCERIN, HIBISCUS SABDARIFFA FLOWER EXTRACT, CENTELLA ASIATICA (GOTU KOLA) LEAF EXTRACT, CAMELLA SINENSIS (WHITE TEA) LEAF EXTRACT, CAMELLA OLEFERA (GREEN TEA) LEAF EXTRACT, ALOE BARBADENSIS LEAF JUICE POWDER, SODIUM HYDROXIDE

PACKAGE LABEL

GLYTONE

ACNE BACK & CHEST TREATMENT SPRAY

ACNE THERAPY

2% SALICYLIC ACID ACNE MEDICATION

GLUCONOLACTONE (PHA)

ALOE

240 mL / 8.0 FL. OZ.